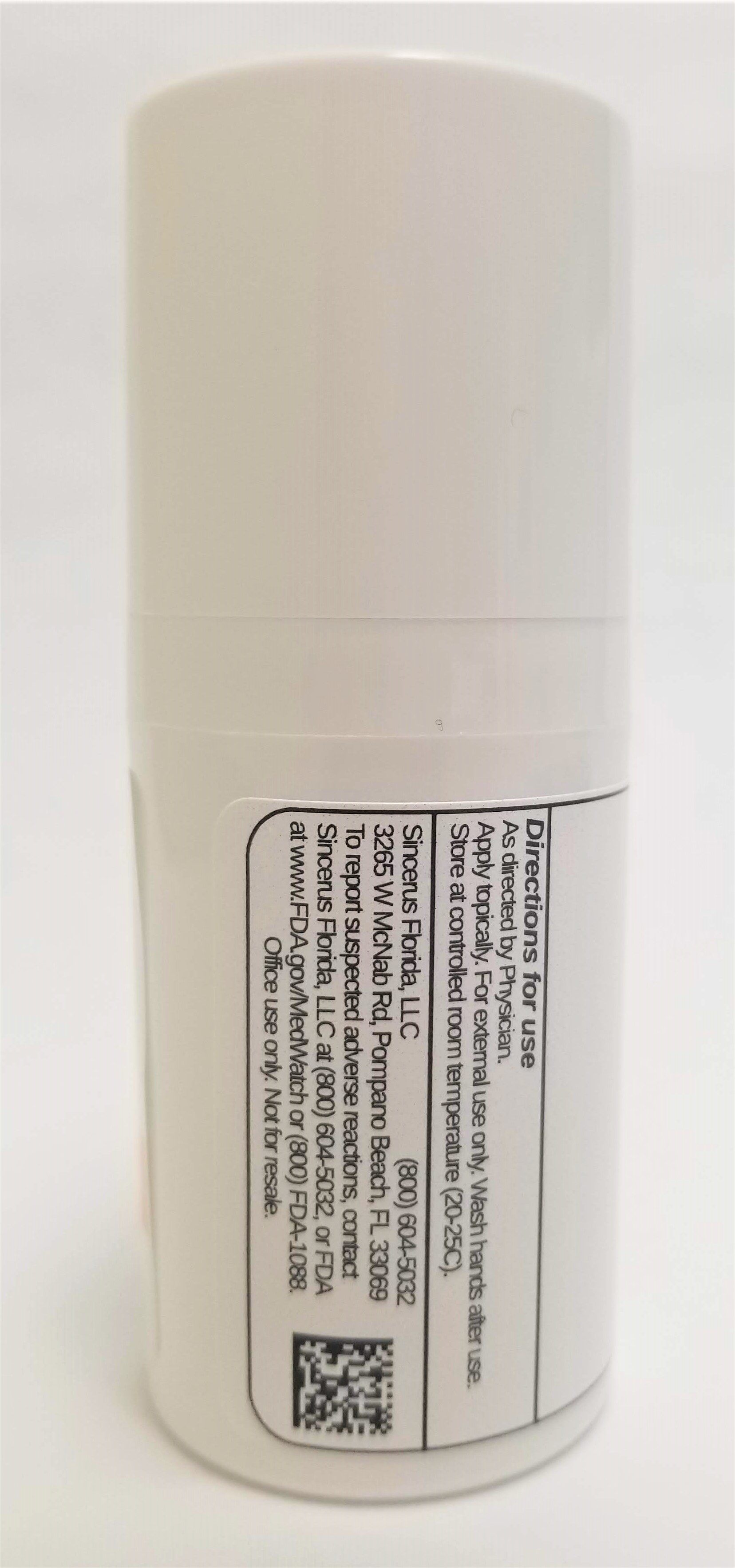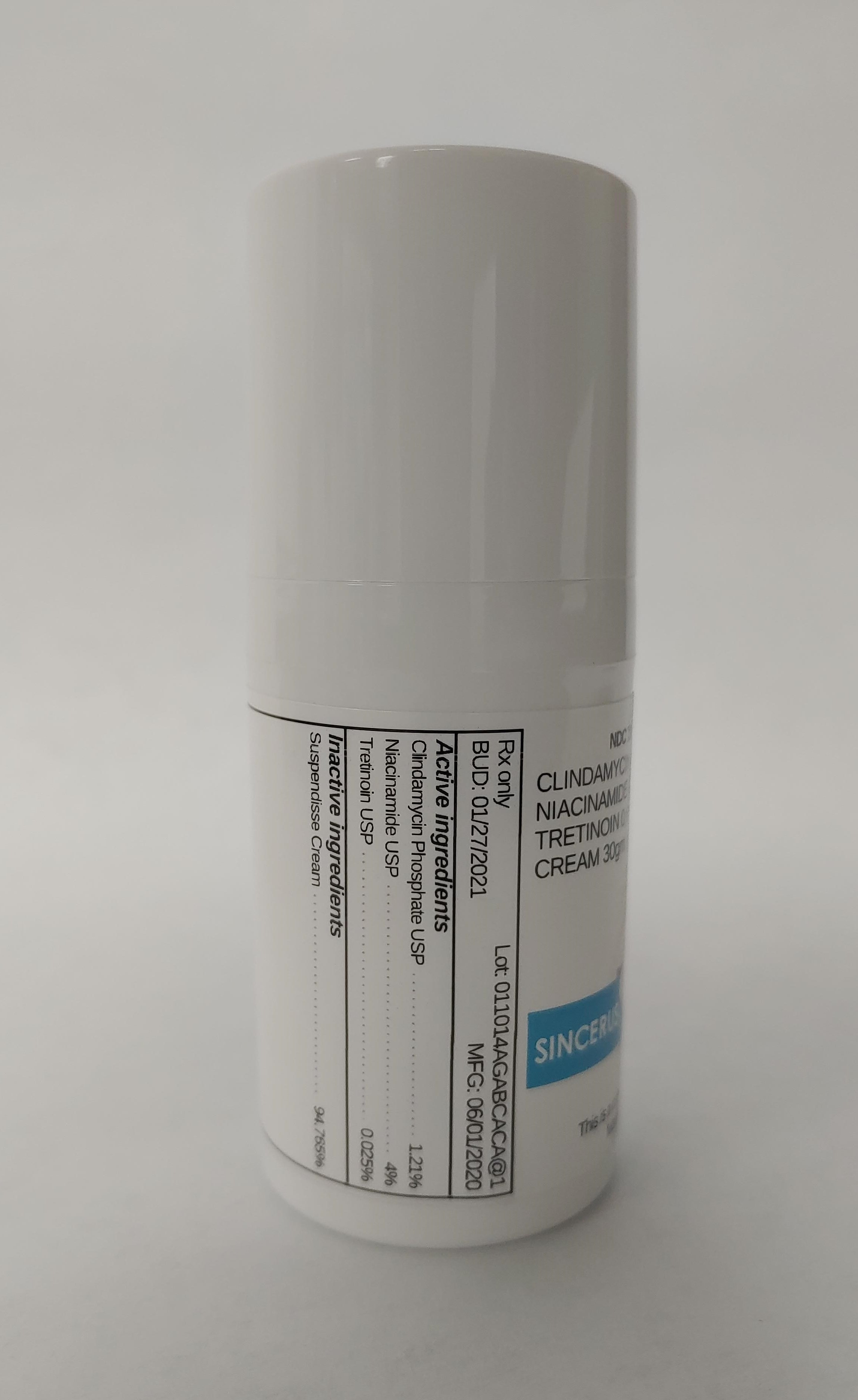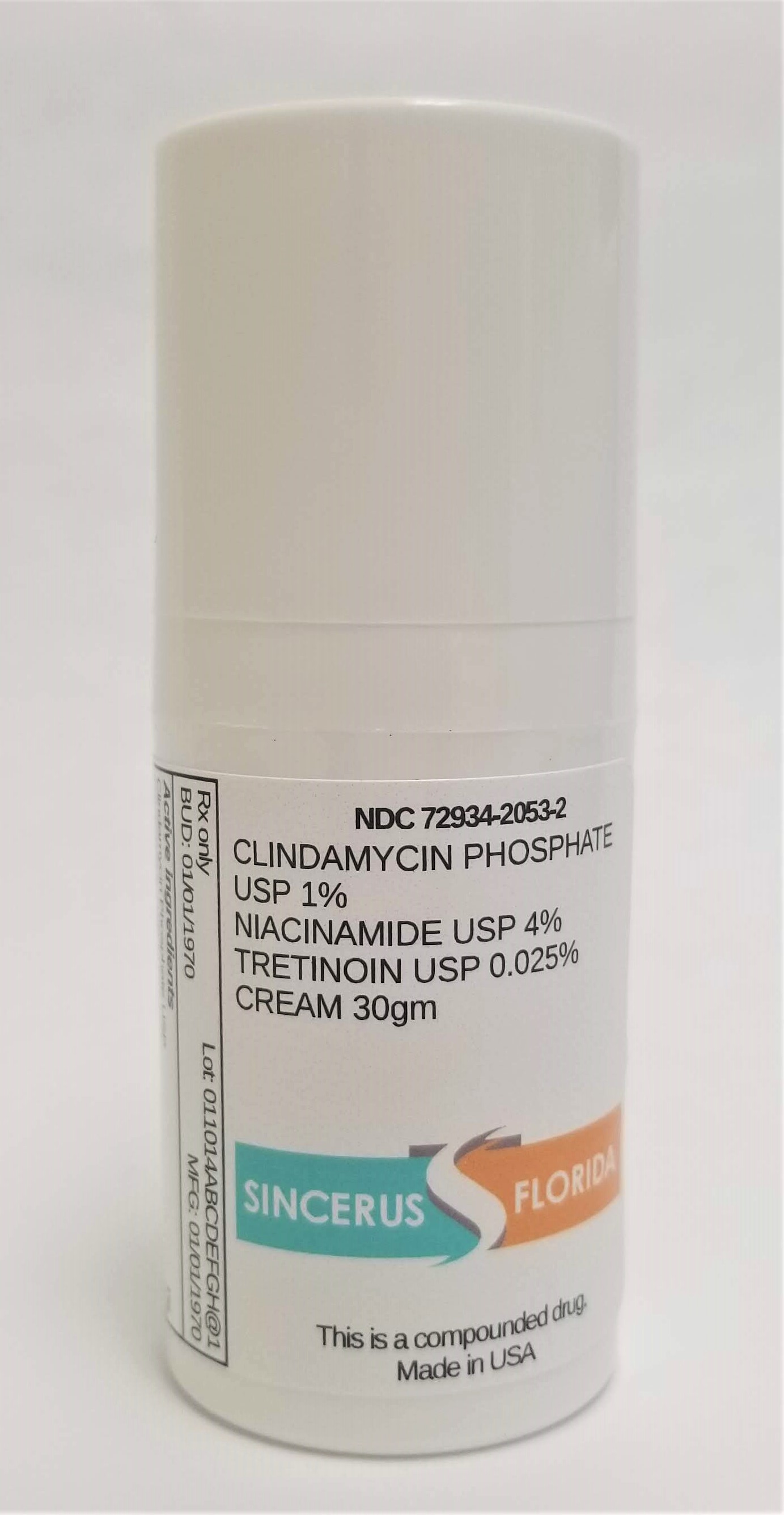 DRUG LABEL: CLINDAMYCIN 1% / NIACINAMIDE 4% / TRETINOIN 0.025%
NDC: 72934-2053 | Form: CREAM
Manufacturer: Sincerus Florida, LLC
Category: prescription | Type: HUMAN PRESCRIPTION DRUG LABEL
Date: 20200603

ACTIVE INGREDIENTS: CLINDAMYCIN PHOSPHATE 1 g/100 g; TRETINOIN 0.025 g/100 g; NIACINAMIDE 4 g/100 g

CLINDAMYCIN 1% / NIACINAMIDE 4% / TRETINOIN 0.025%